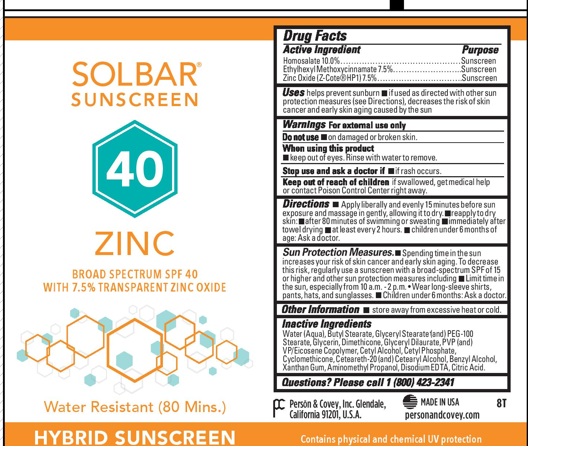 DRUG LABEL: Solbar Zinc SPF38
NDC: 0096-0688 | Form: CREAM
Manufacturer: Person and Covey
Category: otc | Type: HUMAN OTC DRUG LABEL
Date: 20251204

ACTIVE INGREDIENTS: HOMOSALATE 0.1015 g/1 g; OCTINOXATE 0.077 g/1 g; ZINC OXIDE 0.077 g/1 g
INACTIVE INGREDIENTS: WATER; ISOBUTYL STEARATE; PEG-100 STEARATE; GLYCERIN; DIMETHICONE; EICOSYL POVIDONE (2 EICOSYL BRANCHES/REPEAT); GLYCERYL DILAURATE; CETYL ALCOHOL; DIETHANOLAMINE CETYL PHOSPHATE; BENZYL ALCOHOL; CYCLOMETHICONE; STEARYL ALCOHOL; XANTHAN GUM; EDETATE SODIUM; ANHYDROUS CITRIC ACID

Solbar Zinc

Indications and use

Helps prevent sunburn.

Purpose

Sunscreen

Keep out of the reach of children

Yes. If swallowed, get medical help or contact a Poison Control Center right away.

Dosage and Administration

Apply liberally and evenly to all sun exposed areas of DRY skin 15 minutes before sun exposure. Reapply after 80 minutes of swimming or sweating and immediately after towel drying. Apply at least every 2 hours. For children under 6 months, ask a physician.

Warnings

For external use only. Do not use on damaged or broken skin. Keep out of eyes. Rinse eyes thoroughly with water to remove. Stop use and ask a physician if rash or irritation develops and lasts. Store away from excessive heat and direct sun.

OTC - ACTIVE INGREDIENT SECTION

Homosalate

Octinoxate

Zinc Oxide

INACTIVE INGREDIENT SECTION

Water

Isobutyl Stearate

PEG-100 Stearate

Glycerin

Dimethicone

PVP/Eicosene Copolymer

Glyceryl Dilaurate

Cetyl Alcohol

DEA Cetyl Phosphate

Benzyl Alcohol

Cyclomethicone

Stearyl Alcohol

Xanthan Gum

Disodium EDTA

Citric Acid